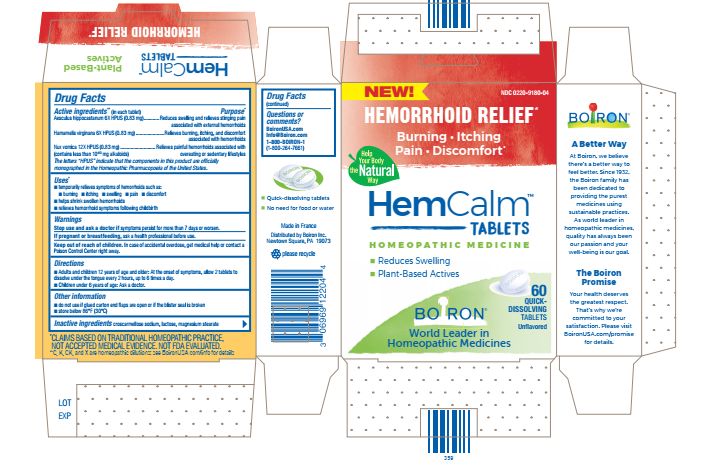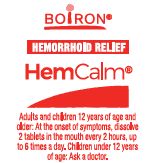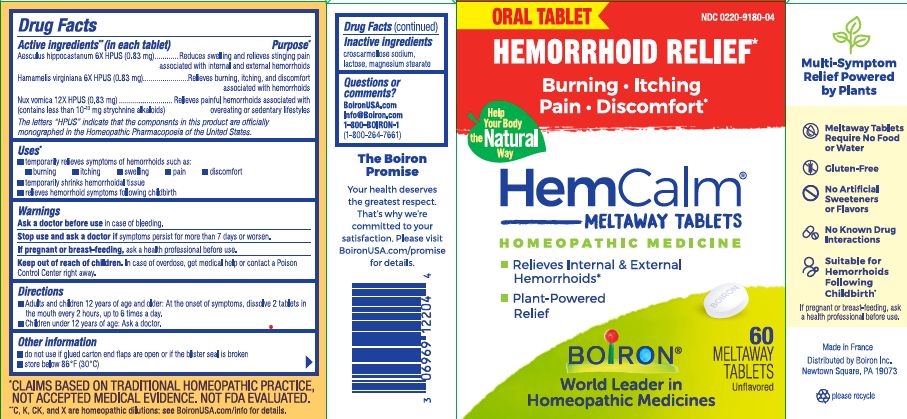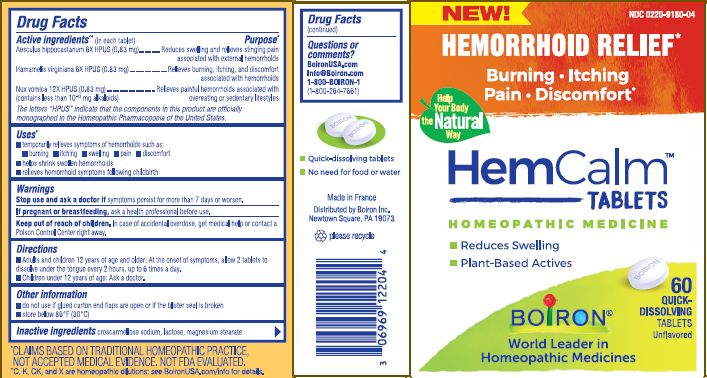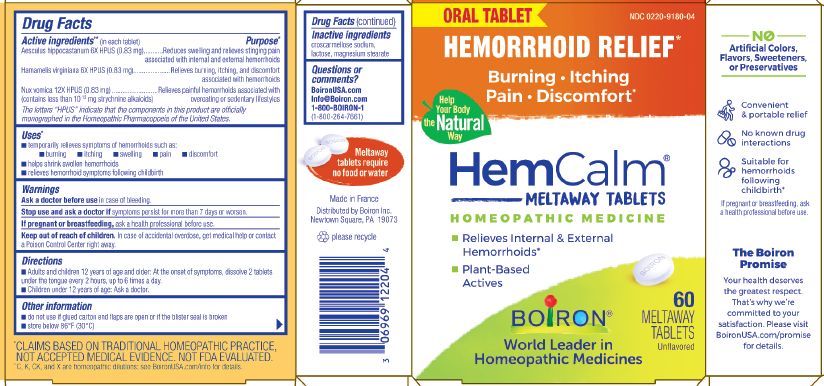 DRUG LABEL: HEMCALM
NDC: 0220-9180 | Form: TABLET
Manufacturer: BOIRON
Category: homeopathic | Type: HUMAN OTC DRUG LABEL
Date: 20240208

ACTIVE INGREDIENTS: HAMAMELIS VIRGINIANA ROOT BARK/STEM BARK 6 [hp_X]/1 1; STRYCHNOS NUX-VOMICA SEED 12 [hp_X]/1 1; HORSE CHESTNUT 6 [hp_X]/1 1
INACTIVE INGREDIENTS: LACTOSE, UNSPECIFIED FORM; MAGNESIUM STEARATE; CROSCARMELLOSE SODIUM

HEMCALM

Active ingredients**

Aesculus hippocastanum 6X HPUS (0.83 mg)

Hamamelis virginiana 6X HPUS (0.83 mg)

Nux vomica 12X HPUS (0.83 mg) (contains less than 10^-13 mg strychnine alkaloids)

The letters "HPUS" indicate that the components in this product are officially monographed in the Homeopathic Pharmacopoeia of the United States.

Purpose*

Aesculus hippocastanum 6X HPUS (0.83 mg) ... Relieves swelling and relieves stinging pain associated with internal and external hemorrhoids

Hamamelis virginiana 6X HPUS (0.83 mg) ... Relieves burning, itching, and discomfort associated with hemorrhoids

Nux vomica 12X HPUS (0.83 mg) ... Relieves painful hemorrhoids associated with overeating and sedentary lifestyles

Uses *

temporarily relieves symptoms of hemorrhoids such as:

- burning
- itching
- swelling
- pain
- discomfort

- temporarily shrinks hemorrhoidal tissue
- relieves hemorrhoid symptoms following childbirth

Ask a doctor before use in case of bleeding.

Stop use and ask a doctor if symptoms persist for more than 7 days or worsen.

PREGNANCY OR BREAST FEEDING

If pregnant or breast-feeding, ask a health professional before use.

Keep out of reach of children. In case of overdose, get medical help or contact a Poison Control Center right away.

DOSAGE AND ADMINISTRATION

Adults and children 12 years of age and older: At the onset of symptoms, dissolve 2 tablets in the mouth every 2 hours, up to 6 times a day.

Children under 12 years of age: Ask a doctor.

do not use if glued carton end flaps are open or if the blister seal is broken

60 MELTAWAY TABLETS Unflavored

store below 86° F (30° C)

Hemorrhoid Relief*

Burning, Itching, Pain, Discomfort*

Relieves Internal & External Hemorrhoids*

Plant-Powered Relief

No known drug interactions

Suitable for hemorrhoids following childbirth*

*CLAIMS BASED ON TRADITIONAL HOMEOPATHIC PRACTICE NOT ACCEPTED MEDICAL EVIDENCE. NOT FDA EVALUATED.
*C,K,CK, and X are homeopathic dilutions: see BoironUSA.com/info for details.

INACTIVE INGREDIENT

croscarmellose sodium, lactose, magnesium stearate

QUESTIONS

1-800-BOIRON-1 (1-800-264-7661)
BoironUSA.com Info@boiron.com
Distributed by Boiron, Inc. Newtown Square, PA 19073